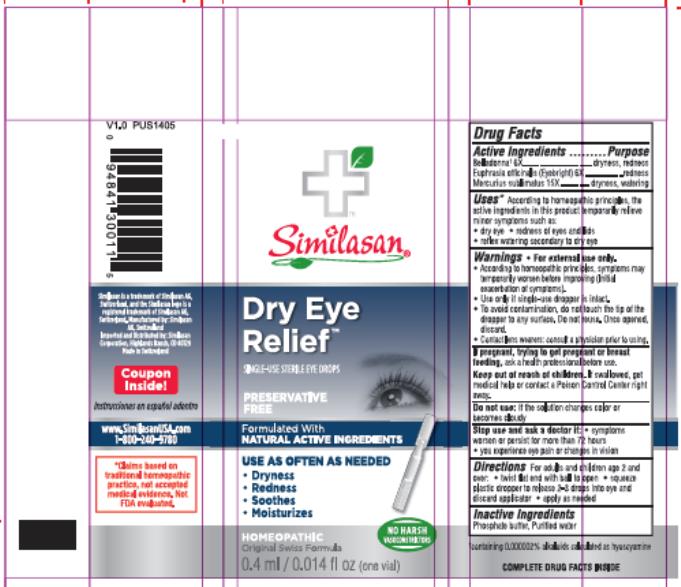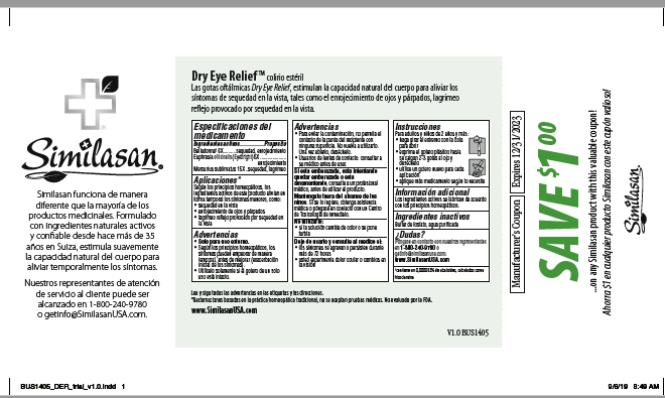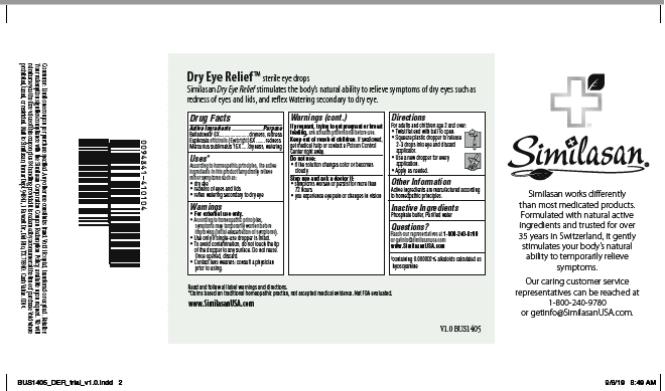 DRUG LABEL: Dry Eye Relief Trial Size 15x
NDC: 53799-376 | Form: SOLUTION/ DROPS
Manufacturer: Similasan AG
Category: homeopathic | Type: HUMAN OTC DRUG LABEL
Date: 20210712

ACTIVE INGREDIENTS: ATROPA BELLADONNA 6 [hp_X]/10 mL; EUPHRASIA STRICTA 6 [hp_X]/10 mL; MERCURIC CHLORIDE 15 [hp_X]/10 mL
INACTIVE INGREDIENTS: WATER; SODIUM NITRATE

Dry Eye Relief Trial Size 15x

Dry Eye Relief Trial Size

Active Ingredient

Belladonna* 6X
*containing 0.000002% alkaloids calculated as hyoscyamine.

Purpose

dryness, redness

Active Ingredient

Euphrasia officinalis (Eyebright) 6X

Purpose

redness

Active Ingredient

Mercurius sublimatus 15X

Purpose

dryness, watering

Uses*

According to homeopathic principles, the active ingredients in this product temporarily relieve minor symptoms such as:

- dry eye
- redness of eyes and lids
- reflex watering secondary to dry eye

Warnings

- For external use only.
- According to homeopathic principles, symptoms may temporarily worsen before improving (Initial exacerbation of symptoms).
- Use only if single-use dropper is intact.
- To avoid contamination, do not touch the tip of the dropper to any surface. Do not reuse. Once opened, discard.
- Contact wearers: consult a physician prior to using.

If pregnant, trying to get pregnant or breast feeding,

ask a health professional before use.

Keep out of reach of children.

If swallowed, get medical help or contact a Poison Control Center right away.

Do not use:

if the solution changes color or becomes cloudy

Stop use and ask a doctor if:

- symptoms worsen or persist for more than 72 hours
- you experience eye pain or changes in vision

Directions

For adults and children age 2 and over:

- twist flat end with ball to open
- squeeze plastic dropper to release 2-3 drops into eye and discard applicator
- apply as needed

Inactive Ingredients

Phosphate buffer, Purified water

Principal Display Panel

Similasan
Dry Eye
Relief
SINGLE-USE STERILE EYE DROPS
Preservative Free
0.4 ml/ 0.014 fl oz (one vial)